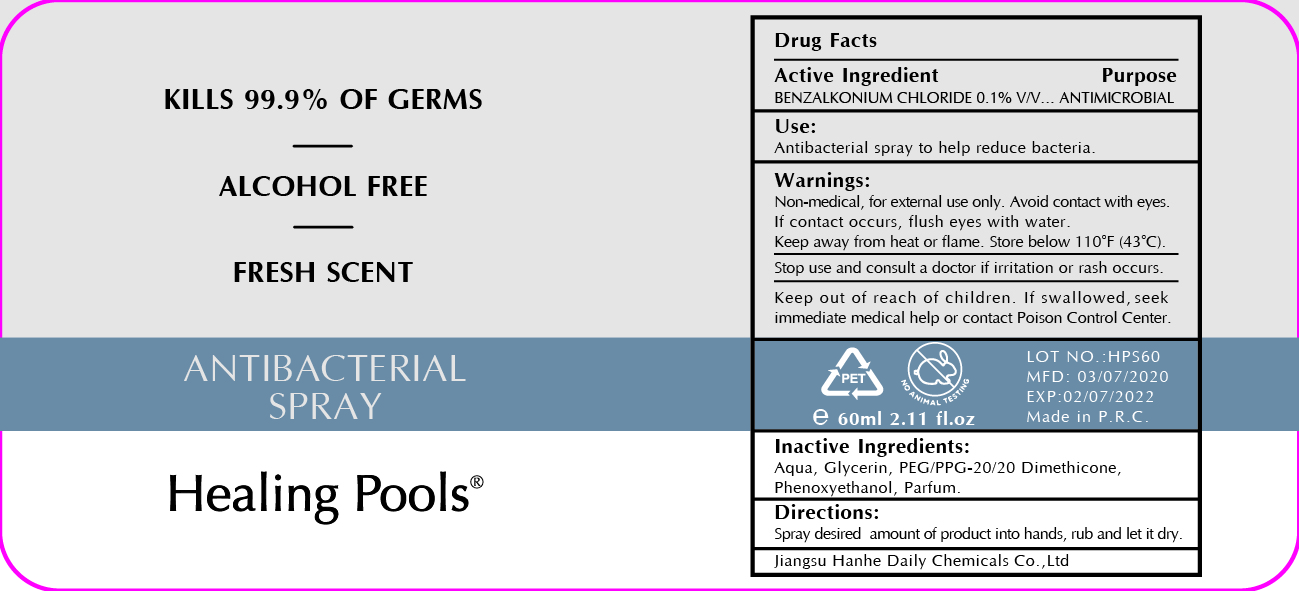 DRUG LABEL: Healing Pools Fresh Scent Antibacterial
NDC: 73027-212 | Form: SPRAY
Manufacturer: JIANGSU HANHE DAILY CHEMICALS CO., LTD.
Category: otc | Type: HUMAN OTC DRUG LABEL
Date: 20211102

ACTIVE INGREDIENTS: BENZALKONIUM CHLORIDE 0.1 g/100 mL
INACTIVE INGREDIENTS: GLYCERIN; PEG/PPG-20/20 DIMETHICONE; WATER; PHENOXYETHANOL

-212 healing pools

Active Ingredient

Benzalkonium Chloride 0.1%

Purpose

Antimicrobial

Use

Antibacterial spray to help reduce bacteria

Warnings

Non Medical. For external use only.

Keep away from heat or flame

Avoid contact with eyes. If contact occurs, flush eyes with water

Stop use and consult a doctor if irritation or rash occurs.

Keep out of reach of children. If swallowed, seek immediate medical help or contact a poison control center

Directions

- Spray desired amount of products into hands, rub and let it dry

Other Information

Store below 110F (43C)

Inactive ingredients

Water, Glycerin, PEG/PEG 20-20 Dimethicone, Phenoxyethanol, Parfum